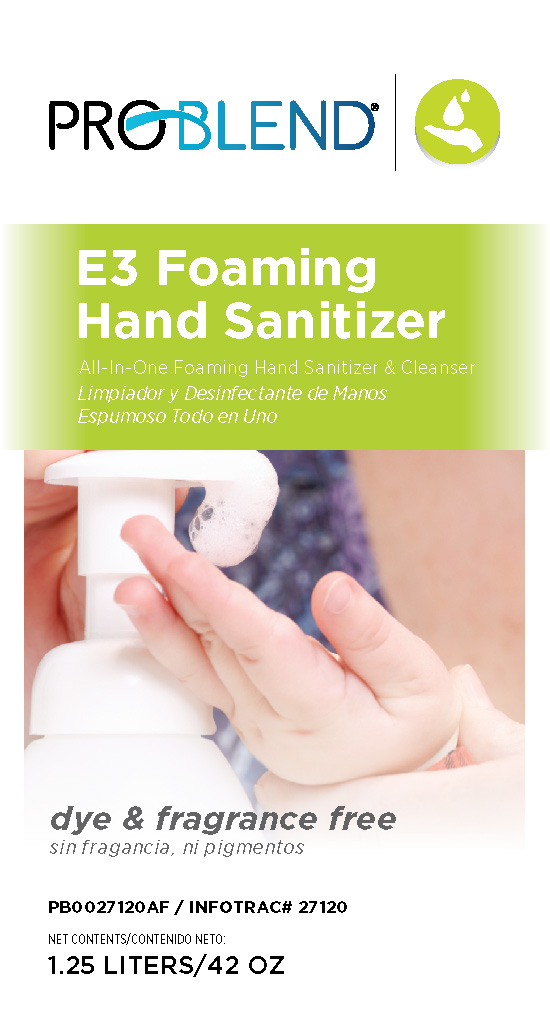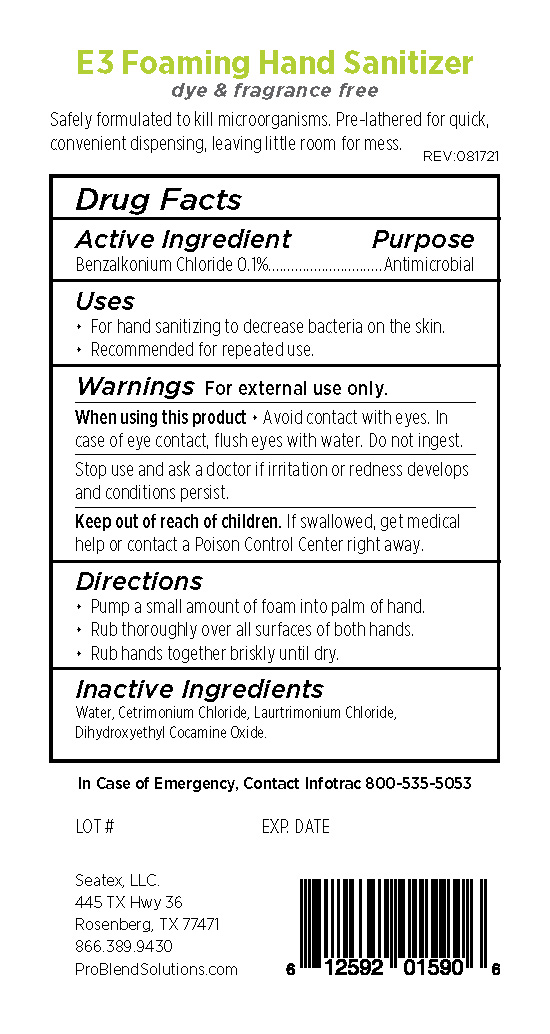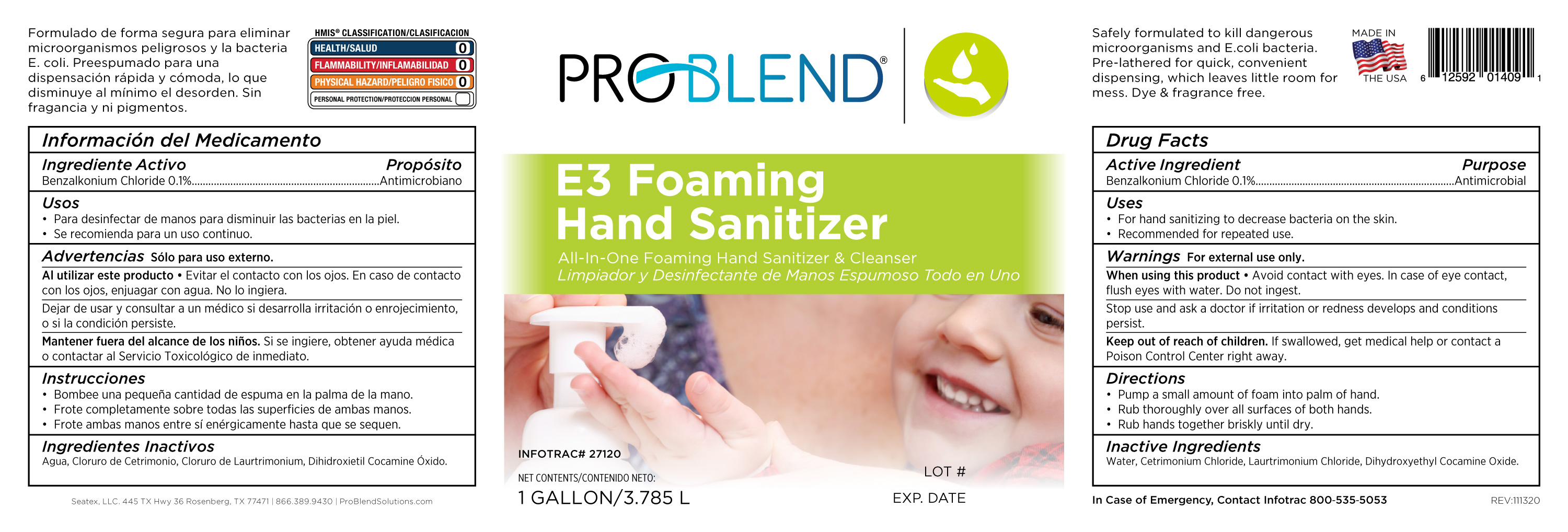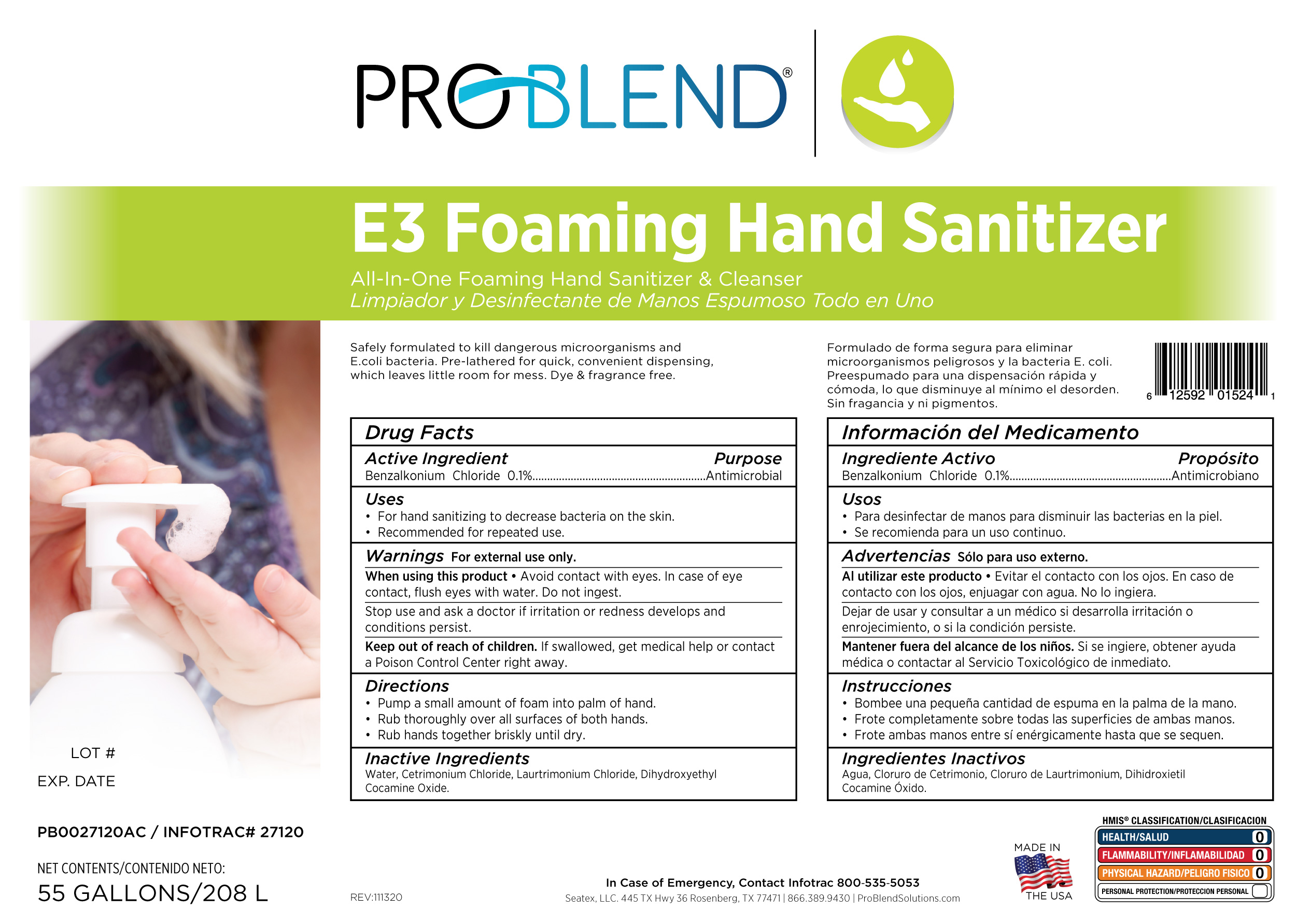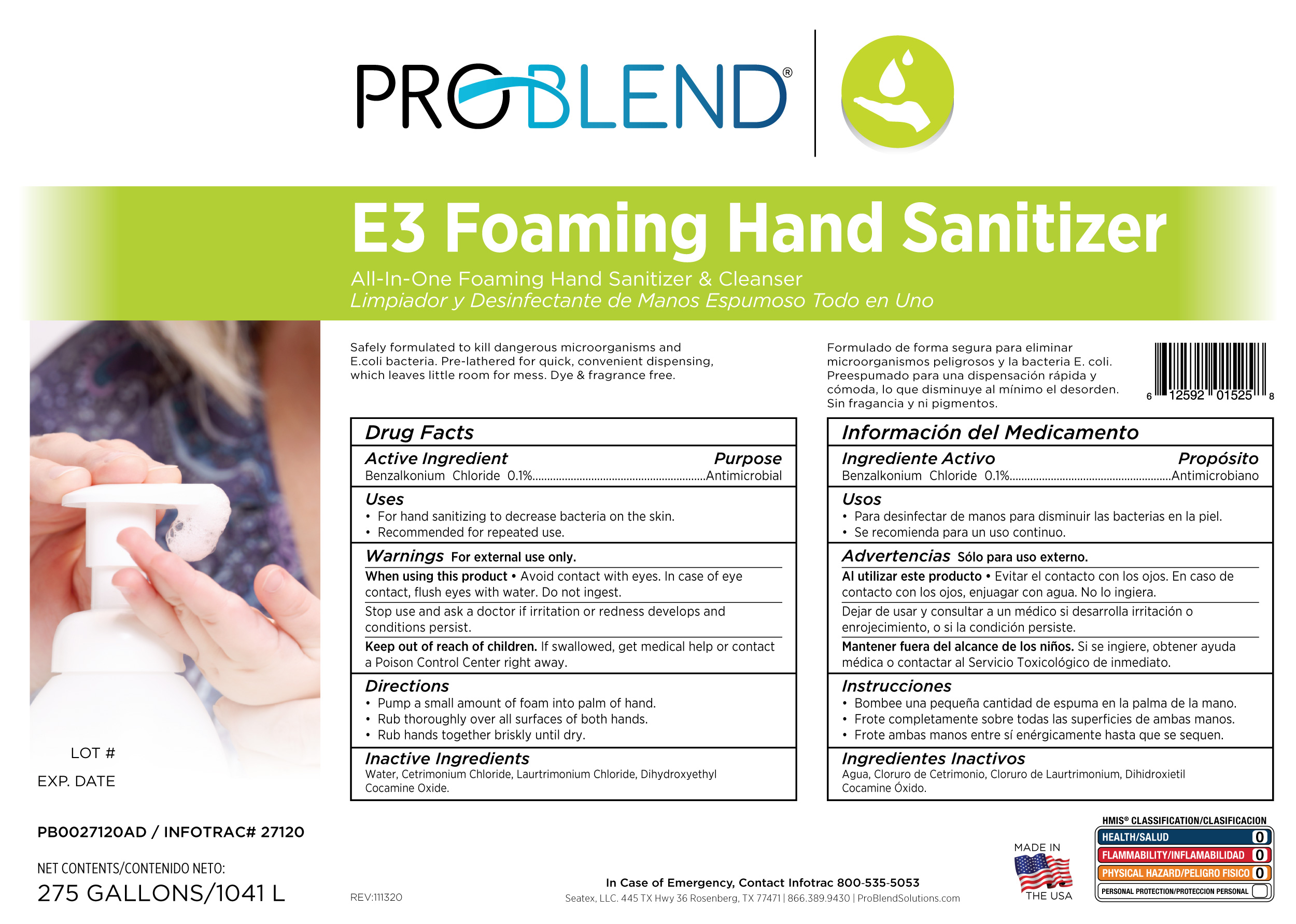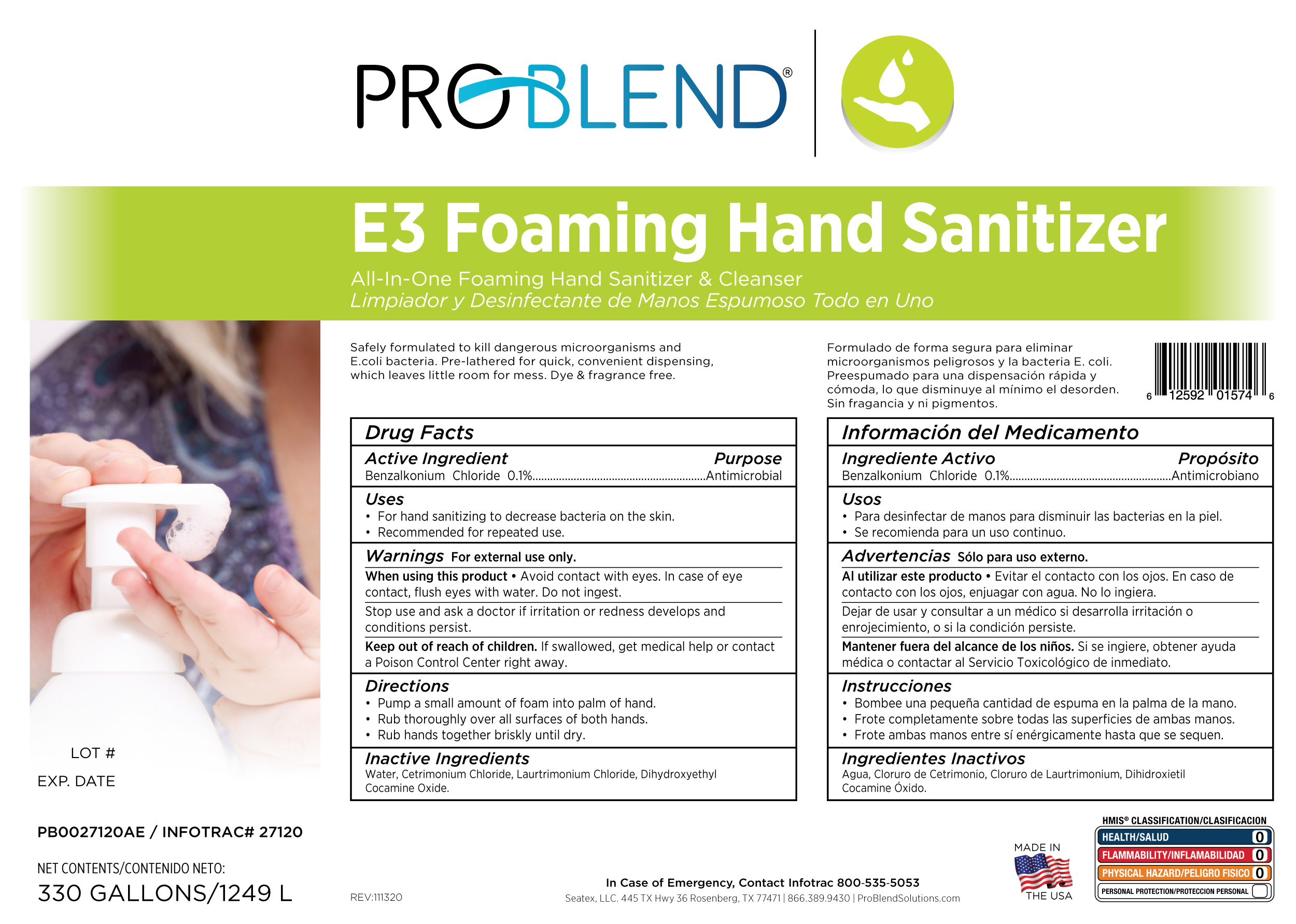 DRUG LABEL: Problend E3 Foaming Hand Sanitizer
NDC: 76250-120 | Form: SOAP
Manufacturer: Seatex, LLC
Category: otc | Type: HUMAN OTC DRUG LABEL
Date: 20220919

ACTIVE INGREDIENTS: BENZALKONIUM CHLORIDE 0.1 g/100 g
INACTIVE INGREDIENTS: WATER; CETRIMONIUM CHLORIDE; LAURTRIMONIUM CHLORIDE; DIHYDROXYETHYL COCAMINE OXIDE

27120 Sanitizer Foam Bulk

Active Ingredient Purpose

Benzalkonium Chloride 0.1%...................Antimicrobial

Uses

For hand sanitizing to decrease bacteria on the skin.

Recommended for repeated use.

When using this product Avoid contact with eyes. In case of eye contact, flush eyes with water. Do not ingest.

Keep out of reach of children. If swallowed, get medical help or contact a Poison Control Center right away.

Directions

Pump a small amount of foam into palm of hand.

Rub thoroughly over all surffaces of both hands

Rub hands together briskly until dry.

Inactive Ingredients

Water, Cetrimonium Chloride, Laurtrimonium Chloride, Dihydroxyethyl Cocamine Oxide

Stop use and ask a doctor if irritation or redness develops and conditions persist.

PURPOSE

Antiseptic, Hand Sanitizer

Warnings For External use only.

PACKAGE LABEL

3.785 L 76250-120-01

PACKAGE LABEL

1249 L 76250-120-30

PACKAGE LABEL

208 L 76250-120-55

PACKAGE LABEL

1041 L 76250-120-75

PACKAGE LABEL

1.25 L Front 76250-120-25

PACKAGE LABEL

1.25 L Back 76250-120-25